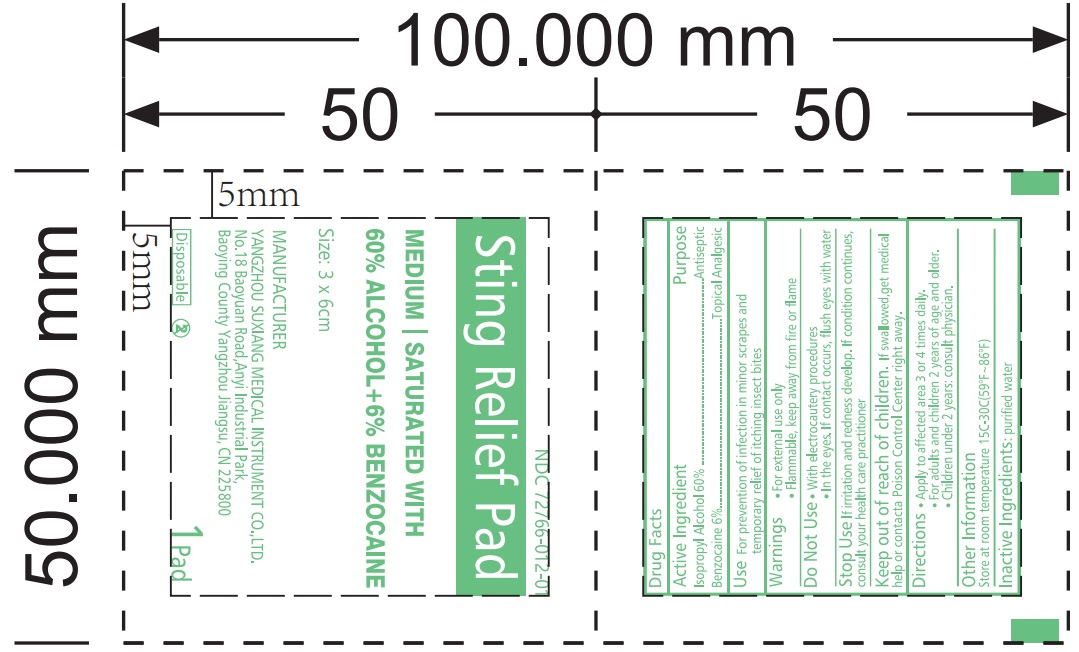 DRUG LABEL: Sting Relief Pad
NDC: 72766-012 | Form: SWAB
Manufacturer: Yangzhou Suxiang Medical Instrument Co., Ltd.
Category: otc | Type: HUMAN OTC DRUG LABEL
Date: 20240305

ACTIVE INGREDIENTS: BENZOCAINE 0.8 g/1 1; ISOPROPYL ALCOHOL 8 g/1 1
INACTIVE INGREDIENTS: WATER

Sting Relief Medicated Pad

ACTIVE INGREDIENT

Benocaine 6% lsopropyl Alcohol 70%

PURPOSE

Topical analgesic

antiseptic

USES

For prevention of infection in minor scrapes andtemporary relief of itching insect bites

WARNINGS

For external use only.
Flammable, keep away from fire or flame.

DO NOT USE

with electrocautery procedures.
In the eyes. If contact occurs, flush eyes with water.

Stop Use lf irritation and redness develop. If condition continues,consult your health care practitioner.

Keep out of reach of children. If swallowed,get medical help or contacta Poison Control Center right away.

Directions

Apply to affected area 3 or 4 times daily.
For adults and children 2 years of age and older.

Children under 2 years:consult physician.

other Information

store at room temperature 15° - 30° C (59° - 86° F)

INACTIVE INGREDIENT

purified water